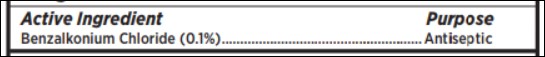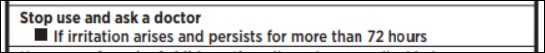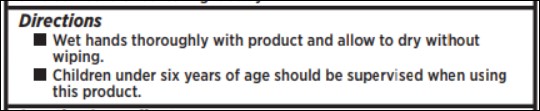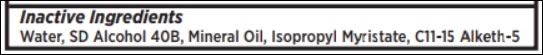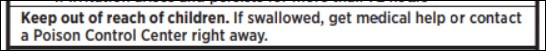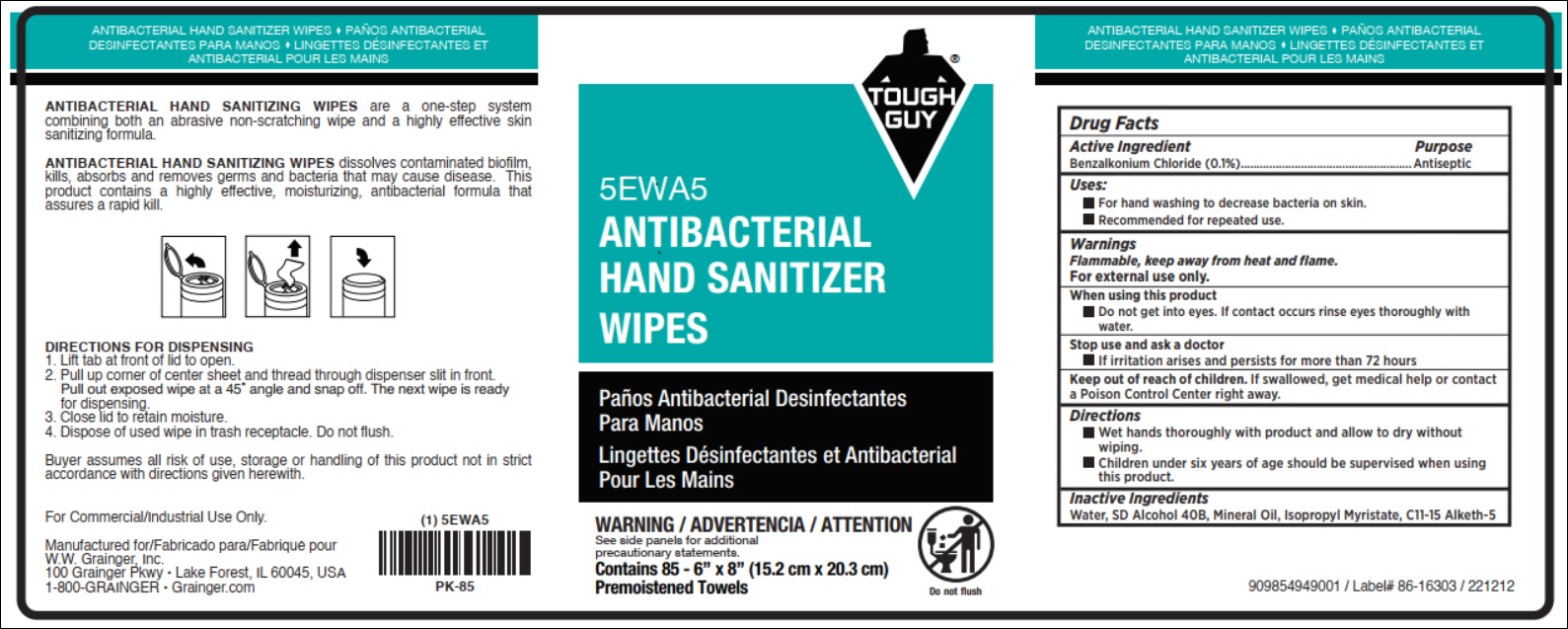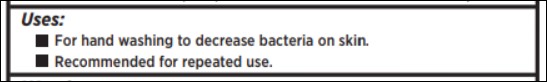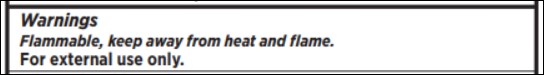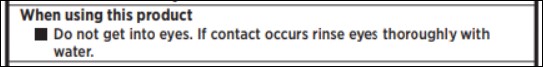 DRUG LABEL: 5EWA5 Antibacterial Hand Sanitizer Wipes
NDC: 40096-1909 | Form: CLOTH
Manufacturer: W.W. Grainger
Category: otc | Type: HUMAN OTC DRUG LABEL
Date: 20241010

ACTIVE INGREDIENTS: BENZALKONIUM CHLORIDE 0.1 g/100 g
INACTIVE INGREDIENTS: ALCOHOL; ISOPROPYL MYRISTATE; WATER; C11-15 PARETH-5; MINERAL OIL

5EWA5 Antibacterial Hand Sanitizer Wipes